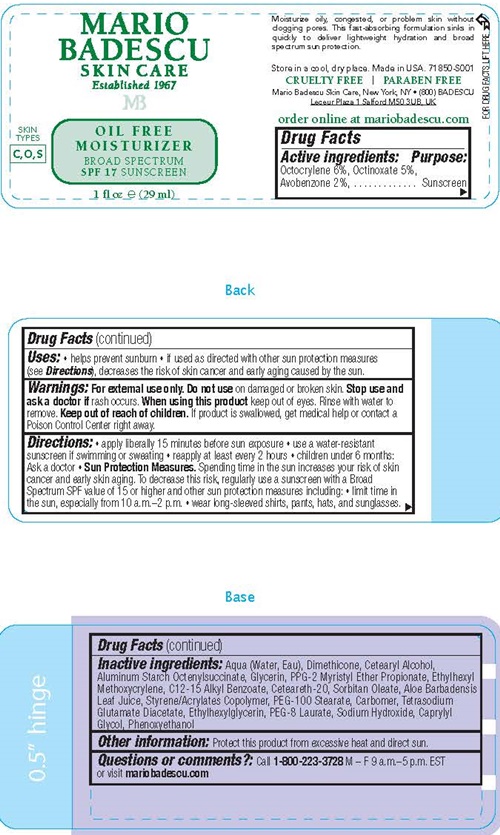 DRUG LABEL: Mario Badescu SPF 17
NDC: 54111-135 | Form: LOTION
Manufacturer: Bentley Laboratories LLC
Category: otc | Type: HUMAN OTC DRUG LABEL
Date: 20240910

ACTIVE INGREDIENTS: AVOBENZONE 1.0 g/29 mL; OCTINOXATE 2.5 g/29 mL; OCTOCRYLENE 3.0 g/29 mL
INACTIVE INGREDIENTS: WATER; DIMETHICONE; CETOSTEARYL ALCOHOL; ALUMINUM STARCH OCTENYLSUCCINATE; GLYCERIN; PPG-2 MYRISTYL ETHER PROPIONATE; ETHYLHEXYL METHOXYCRYLENE; ALKYL (C12-15) BENZOATE; POLYOXYL 20 CETOSTEARYL ETHER; SORBITAN MONOOLEATE; ALOE VERA LEAF; STYRENE/ACRYLAMIDE COPOLYMER (MW 500000); PEG-100 STEARATE; CARBOXYPOLYMETHYLENE; TETRASODIUM GLUTAMATE DIACETATE; ETHYLHEXYLGLYCERIN; PEG-8 LAURATE; SODIUM HYDROXIDE; CAPRYLYL GLYCOL; PHENOXYETHANOL

Mario Badescu Oil Free Moisturizer SPF 17

Drug Facts Active ingredients

Avobenzone 2.0%
Octinoxate 5%
Octocrylene 6%

Purpose

Sunscreen

Uses

- helps prevent sunburn
- If used as directed with other sun protection measures (see Directions), decreases the risk of skin cancer and early aging caused by the sun.

Warnings

For external use only.

Do not use on damaged or broken skin.

Stop use and ask a doctor if rash occurs.

When using this product keep out of eyes. Rinse with water to remove

Keep out of reach of children.

If product is swallowed, get medical help or contact a Poison Control Center right away.

Directions

- apply liberally 15 minutes before sun exposure
- use a water-resistant sunscreen if swimming or sweating
- reapply at least every 2 hours
- children under 6 months: Ask a doctor

Sun Protection Measures. Spending time in the sun increases your risk of skin cancer and early skin aging. To decrease this risk, regularly use a sunscreen with a Broad Spectrum SPF value of 15 or higher and other sun protection measures including:

- limit time in the sun, especially from 10 a.m. - 2 p.m.
- wear long-sleeved shirts, pants, hats, and sunglasses.

Inactive ingredients

Aqua (Water, Eau), Dimethicone, Cetearyl Alcohol, Aluminum Starch Octenylsuccinate, Glycerin, PPG-2 Myristyl Ether Propionate, Ethylhexyl Methoxycrylene, C12-15 Alkyl Benzoate, Ceteareth-20, Sorbitan Oleate, Aloe Barbadensis Leaf Juice, Styrene/Acrylates Copolymer, PEG-100 Stearate, Carbomer, Tetrasodium Glutamate Diacetate, Ethylhexlglycerin, PEG-8 Laurate, Sodium Hydoxide, Caprylyl Glycol, Phenoxyethanol

Other information

Protect this product from excessive heat and direct sun.

Questions or comments?

Call 1-800-223-3728 M - F 9 a.m. - 5 p.m. EST or visit mariobadescu.com

Mario Badescu Oil Free Moisturizer SPF 17 product label

MARIO
BADESCU
SKIN CARE
Established 1967
MB
OIL FREE
MOISTURIZER
BROAD SPECTRUM
SPF 17 SUNSCREEN

SKIN TYPES - C, O, S,

1 fl oz (29 ml)

Made in the USA. 71849-J001
CRUELTY FREE l PARABEN FREE
Mario Badescu Skin Care, New York, NY • (800) BADESCU
Leceur Plaza 1 Salford M50 3UB, UK

order online at mariobadescu.com

res